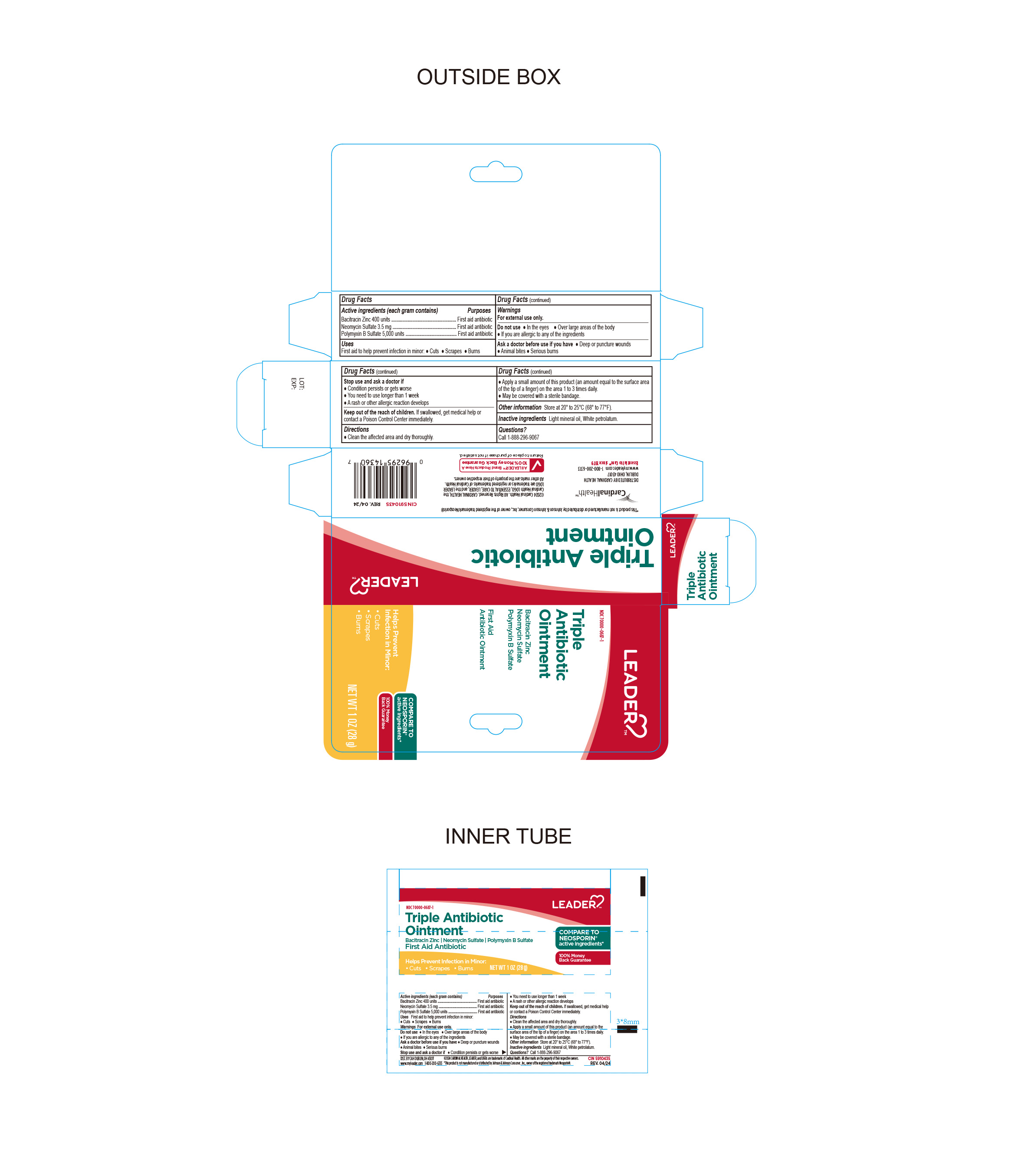 DRUG LABEL: Leader Triple antibiotic
NDC: 70000-0687 | Form: OINTMENT
Manufacturer: Cardinal Health 110 dba LEADER
Category: otc | Type: HUMAN OTC DRUG LABEL
Date: 20240906

ACTIVE INGREDIENTS: BACITRACIN ZINC 400 [USP'U]/1 g; NEOMYCIN SULFATE 3.5 mg/1 g; POLYMYXIN B SULFATE 5000 [USP'U]/1 g
INACTIVE INGREDIENTS: WHITE PETROLATUM; LIGHT MINERAL OIL

Leader Triple Antibiotic Ointment

Active Ingredient

Bacitracin zinc 400 Units

Purpose

First Aid Antibiotic

Active Ingredient

Neomycin Sulfate 3.5mg

Purpose

First Aid Antibiotic

Active Ingredient

Polymixin B Sulfate 5000 units

Purpose

First Aid Antibiotic

Uses

First Aid to help prevent infection in minor

- Cuts
- Scrapes
- Burns

Warnings

For external use only. Do not use:

- In eyes
- Over large areas of the body
- If you are allergic to any of the ingredients

Ask a Doctor before Use

Ask Doctor before use if you have:

- Deep or puncture wouns
- Animal bites
- Serious burns

Stop Use and ask a Doctor if:

- Condition persists or gets worse
- You need to use longer than 1 week
- A rash or other allergic reaction develops

Keep out of Reach of Children

If Swallowed, get medical help or contact a Poison Control Center immediately.

Directions

- Clean the affected area and dry thoroughly
- Apply a small amount of this product (an amount equal to the surface area of the tip of a finger) on the area 1 to 3 times daily
- May be covered with a sterile bandage

Other Information

- Store at 20° to 25°C (68° to 77°F)

Inactive Ingredient:

Light mineral oil, white Petrolatum

Questions?

Call 1-888-296-9067

Distributed By:

Cardinal Health

Dublin, Ohio 43017

www.myleader.com

1-800-200-6313

Essential to care since 1979

©2024 Cardinal Health. All rights reserved. Cardinal Health The Cardinal Health LOGO, ESSENTIAL TO CARE, LEADER, and the LEADER LOGO are trademarks or registered trademarks of Cardinal Health. All other marks are the property of their respective owners.

This product is not manufactured or distributed by Johnson & Johnson Consumer, Inc. Owner of Registered Trademark Neosporin.